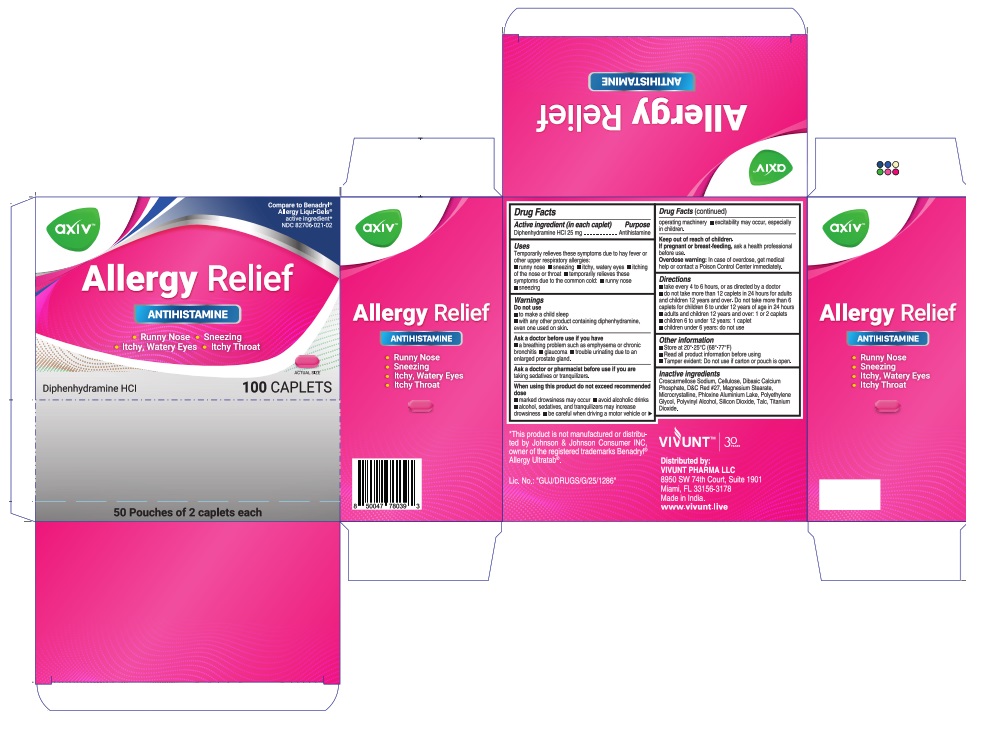 DRUG LABEL: AXIV Allergy Relief
NDC: 82706-021 | Form: TABLET
Manufacturer: VIVUNT PHARMA LLC
Category: otc | Type: HUMAN OTC DRUG LABEL
Date: 20240709

ACTIVE INGREDIENTS: DIPHENHYDRAMINE HYDROCHLORIDE 25 mg/1 1
INACTIVE INGREDIENTS: MAGNESIUM STEARATE; CALCIUM PHOSPHATE, DIBASIC, ANHYDROUS; MICROCRYSTALLINE CELLULOSE; SILICON DIOXIDE; TALC; TITANIUM DIOXIDE; POLYVINYL ALCOHOL, UNSPECIFIED; D&C RED NO. 27; POLYETHYLENE GLYCOL, UNSPECIFIED; ALUMINUM OXIDE; CROSCARMELLOSE SODIUM

AXIV Allergy Relief

Drug Facts

ACTIVE INGREDIENT

Active Ingrediente (in each caplet) --------------- Purpose

Diphenhydramine HCl 25 mg ------------------------- Antihistamine

Uses

Temporarily relieves these symptoms due to have fever or other upper respiratory allergies:

- runny nose
- sneezing
- itchy, watery eyes
- itching of the nose throat
- temporarily relieves these symptoms due to the common cold:
- runny nose
- sneezing

Warnings

Do not use

- to make a child sleep
- with any other product containing diphenhydramine, even one used on skin.

Ask a doctor before use if you have

- a breathing problem such as emphysema or chronic bronchitis
- glaucoma
- trouble urinating due to an enlarged prostate gland.

Ask a doctor or pharmacist before use if you are

taking sedatives or tranquilizers.

When using this product do not exceed recommended dose

- marked drowsiness may occur
- avoid alcoholic drinks
- alcohol, sedatives, and tranquilizers may increase drowsiness
- be careful when driving motor vehicle or operating machinery
- excitability may occur, especially in children.

Keep out of reach of children

If pregnant or breast-feeding

ask a health professinal before use.

Overdose warning

In case of overdose, get medical help or contact a Poison Control Center immediately.

Directions

take every 4 to 6 hours, or as directed by a doctor

do not take more than 12 caplets in 24 hours for adults and children 12 years and over. Do not take more than 6 caplets for children 6 to under 12 years of age in 24 hours

- adults and children 12 years and over 1 or 2 caplets
- children 6 to under 12 years 1 caplet
- children under 6 years do not use

Other information

- Store at 20°-25°C (68°-77°F)
- Read all product information before using
- Tamper evident: Do not use if carton or pouch is open.

Inactive Ingredients

Croscarmellose Sodium, Cellulose, Dibasic Calcium Phosphate, D&C Red #27, Magnesium Stereate, Microcrystalline, Phloxine Aluminium Lake, Polyethylene Glycol, Polyvinyl Alcohol, Silicon Dioxide, Talc, Titanium Dioxide.

PACKAGE LABEL

Compare to Benadryl® Allergy Liqui-Gels®

active ingredient*

NDC 82706-021-02

AXIV Allergy Relief

Antihistamine

Runny Nose
Sneezing
Itchy, Watery Eyes
Itchy Throat

Diphenhydramine HCl

100 CAPLETS